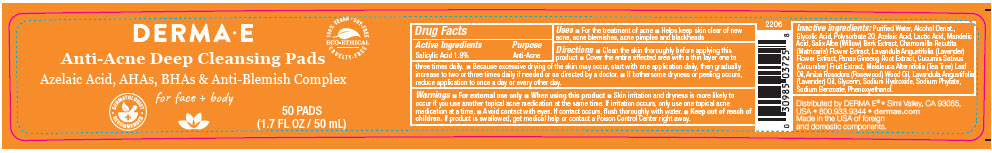 DRUG LABEL: Derma E Acne Cleansing Pads
NDC: 54108-3725 | Form: CLOTH
Manufacturer: derma e
Category: otc | Type: HUMAN OTC DRUG LABEL
Date: 20240528

ACTIVE INGREDIENTS: SALICYLIC ACID 190 mg/1 mL
INACTIVE INGREDIENTS: WATER; ALCOHOL; GLYCOLIC ACID; POLYSORBATE 20; AZELAIC ACID; LACTIC ACID, DL-; MANDELIC ACID; SALIX ALBA BARK; CHAMOMILE; LAVANDULA ANGUSTIFOLIA SUBSP. ANGUSTIFOLIA FLOWER; ASIAN GINSENG; CUCUMBER; TEA TREE OIL; ROSEWOOD OIL; LAVENDER OIL; GLYCERIN; SODIUM HYDROXIDE; PHYTATE SODIUM; SODIUM BENZOATE; PHENOXYETHANOL

Derma E Acne Cleansing Pads

Drug Facts

Active Ingredients

Salicylic Acid 1.9%

Purpose

Anti-Acne

Uses

- For the treatment of acne
- Helps keep skin clear of new acne, acne blemishes, acne pimples and blackheads

Directions

- Clean the skin thoroughly before applying this product
- Cover the entire affected area with a thin layer one to three times daily.
- Because excessive drying of the skin may occur, start with one application daily, then gradually increase to two or three times daily if needed or as directed by a doctor.
- If bothersome dryness or peeling occurs, reduce application to once a day or every other day.

Warnings

- For external use only

- When using this product
- Skin irritation and dryness is more likely to occur if you use another topical acne medication at the same time. If irritation occurs, only use one topical acne medication at a time.
- Avoid contact with eyes. If contact occurs, flush thoroughly with water.

- Keep out of reach of children. If product is swallowed, get medical help or contact a Poison Control Center right away.

Inactive ingredients:

Purified Water, Alcohol Denat., Glycolic Acid, Polysorbate 20, Azelaic Acid, Lactic Acid, Mandelic Acid, Salix Alba (Willow) Bark Extract, Chamomilla Recutita (Matricaria) Flower Extract, Lavandula Angustifolia (Lavender) Flower Extract, Panax Ginseng Root Extract, Cucumis Sativus (Cucumber) Fruit Extract, Melaleuca Alternifolia (Tea Tree) Leaf Oil, Aniba Rosodora (Rosewood) Wood Oil, Lavandula Angustifolia (Lavender) Oil, Glycerin, Sodium Hydroxide, Sodium Phytate, Sodium Benzoate, Phenoxyethanol.

Distributed by DERMA E® • Simi Valley, CA 93065,
USA

PRINCIPAL DISPLAY PANEL - 50 mL Jar Label

DERMA•E

Anti-Acne Deep Cleansing Pads

Azelaic Acid, AHAs, BHAs & Anti-Blemish Complex
for face + body

• DERMATOLOGIST •
RECOMMENDED

100% VEGAN • SOY-FREE
ECO-ETHICAL
CRUELTY-FREE

50 PADS
(1.7 FL OZ / 50 mL)